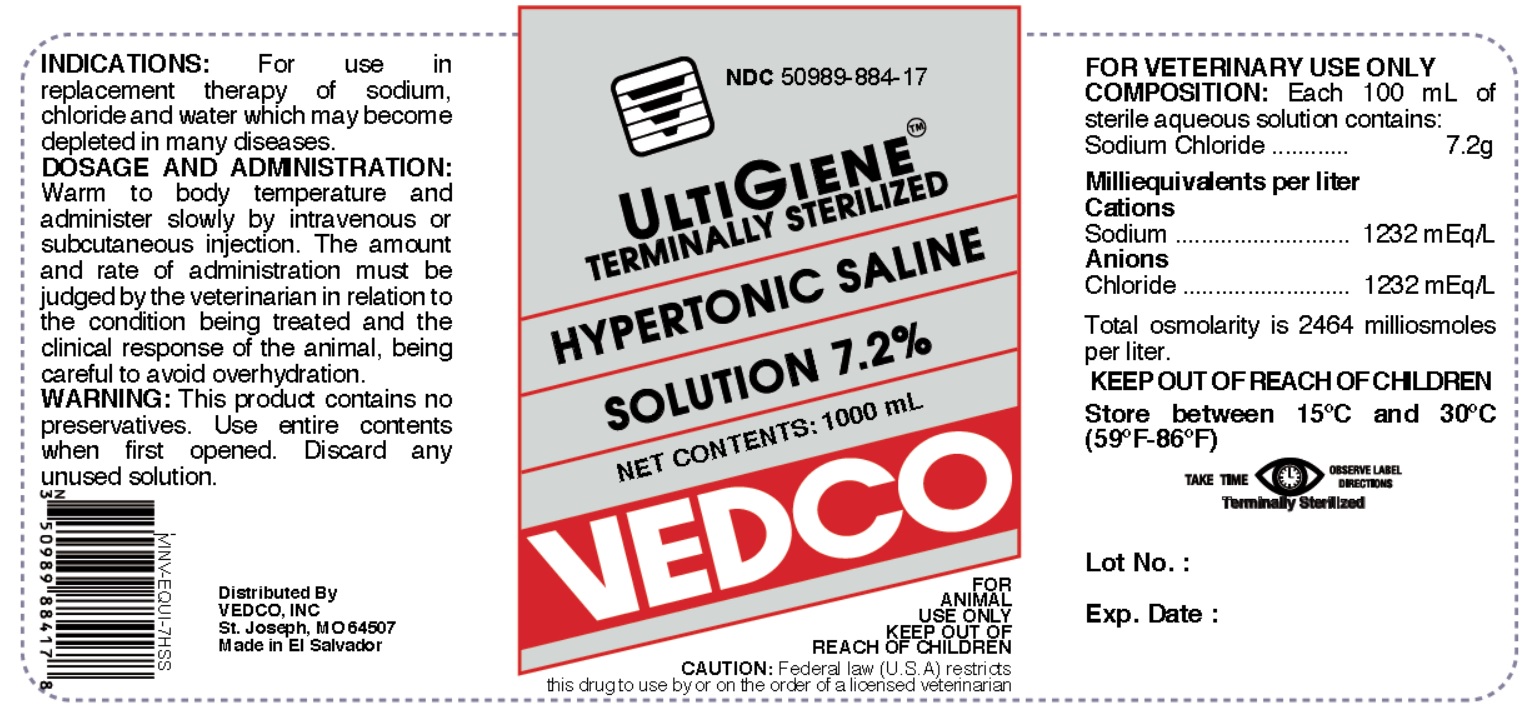 DRUG LABEL: Hypertonic Saline 7.2 %
NDC: 50989-884 | Form: INJECTION, SOLUTION
Manufacturer: Vedco
Category: animal | Type: PRESCRIPTION ANIMAL DRUG LABEL
Date: 20200115

ACTIVE INGREDIENTS: SODIUM CHLORIDE 7.2 g/100 mL

DESCRIPTION

HYPERTONIC SALINE 7.2 %- hypertonic saline 7.2 % injection, solution

Vedco

Disclaimer: This drug has not been found by FDA to be safe and effective, and this labeling has not been approved by FDA.

Hypertonic Saline Solution 7.2%

Sterile - Preservative Free

KEEP OUT OF REACH OF CHILDREN

ACTIVE INGREDIENT

Each 100 mL of sterile aqueous solution contains:

Sodium Chloride.................................................7.2 g

Milliequivalents per liter:

Cations Sodium.......................................1232 mEq/L
Anions Chloride......................................1232 mEq/L

Total osmolarity is 2464 milliosmoles per litter.

INDICATION

For use in replacement therapy of sodium, chloride and water which may become depleted in many diseases.

DOSAGE AND AND ADMINISTRATION

50 to 100 mL per lb bodyweight. Warm to body temperature and administer slowly by intravenous or subcutaneous injection. The amount and rate of administration must be judged by the veterinarian in relation to the condition being treated and the clinical response of the animal, being careful to avoid overhydration.

CAUTION

This product contains no preservatives. Do not use if solution is not clear. Use entire contents when first opened. Discard any unused solution.

Federal law restricts this drug to use by or on the order of a licensed veterinarian.

STORAGE

Store between 15° C - 30° C (59°F - 86°F).

INFORMATION FOR OWNERS/CAREGIVERS

Distributed By

VEDCO, INC.

St. Joseph, MO 64507

Made in El Salvador

Net Contents: 1000 mL

TABLE
CONTENTS | NDC | VINV #
1000 mL | 50989-884-17 | VINV-EQUI-7HSS

PRINCIPAL DISPLAY PANEL

NDC 50989-884-17

ULTIGIENE

TERMINALLY STERILIZED

HYPERTONIC SALINE SOLUTION 7.2%

NET CONTENTS: 1000 mL

VEDCO

FOR ANIMAL USE ONLY

KEEP OUT OF REACH OF CHILDREN

CAUTION: Federal Law (U.S.A) restricts this drug to use by or on the order of a licensed veterinarian